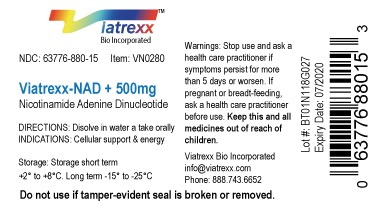 DRUG LABEL: Viatrexx-NAD Plus
NDC: 63776-880 | Form: POWDER
Manufacturer: VIATREXX BIO INCORPORATED
Category: other | Type: DIETARY SUPPLEMENT
Date: 20190319

ACTIVE INGREDIENTS: Nadide 1 mg/1 mg

NAD Plus

STATEMENT OF IDENTITY

Description: Viatrexx-NAD + is 500 mg of powdered NICOTINAMIDE ADENINE DINUCLEOTIDE in a 10 mL vial.
References upon request

HEALTH CLAIM

Viatrexx-NAD + supports Cell Nourishment, Cellular support & energy.

WARNINGS

Warnings: Stop use and ask a health care practitioner if symptoms persist for more than 5 days or worsen. If pregnant or breastfeeding, ask a health care practitioner before use.

DOSAGE AND ADMINISTRATION

Directions: Dissolve in water and take orally

SAFE HANDLING WARNING

Storage short term +2 to +8° C (35 to 46° F), Long term -15 to -25° C (5 to -13° F).
Do not use if a new product’s tamper-evident seal is broken or removed.
To report SUSPECTED ADVERSE REACTIONS, contact the FDA at 1-800-FDA-1088 or www.fda.gov/medwatch
Distributed by Viatrexx Bio Incorporated
Newark, DE, USA, 19713
Manufactured by
8046255 Canada Inc
Beloeil, Qc, J3G 6S3
Date of last revision March 2019
For questions and comments
Info@Viatrexx.com
www.Viatrexx.com

PACKAGE LABEL.PRINCIPAL DISPLAY PANEL

NDC: 63776-880-15
Item: VN0280
Viatrexx Bio Incorporated
Viatrexx-NAD +
Box of 1 X 10 mL vial
For Oral Use
Expiry date: Lot #:
Manufactured for:
Viatrexx Bio Incorporated Newark, DE, USA, 19713
www.Viatrexx.com
Ingredients, homeopathic
See insert or www.viatrexx.com